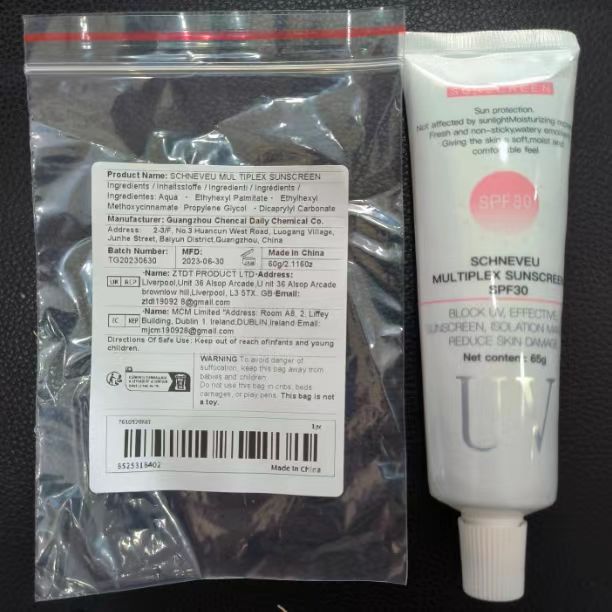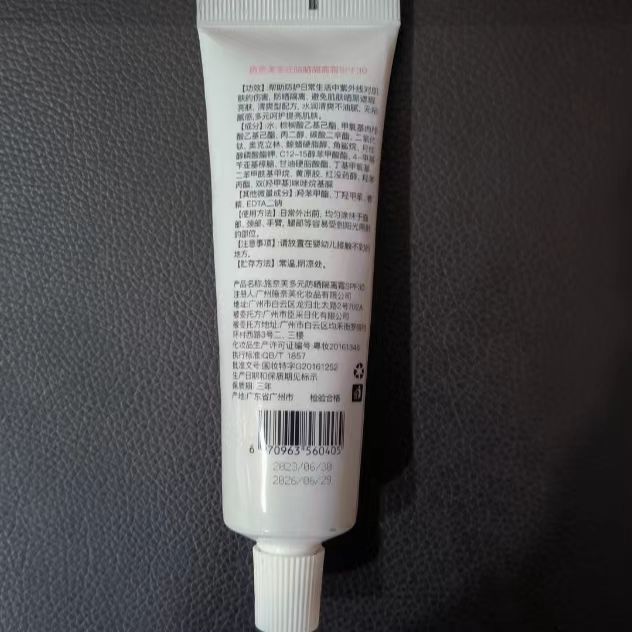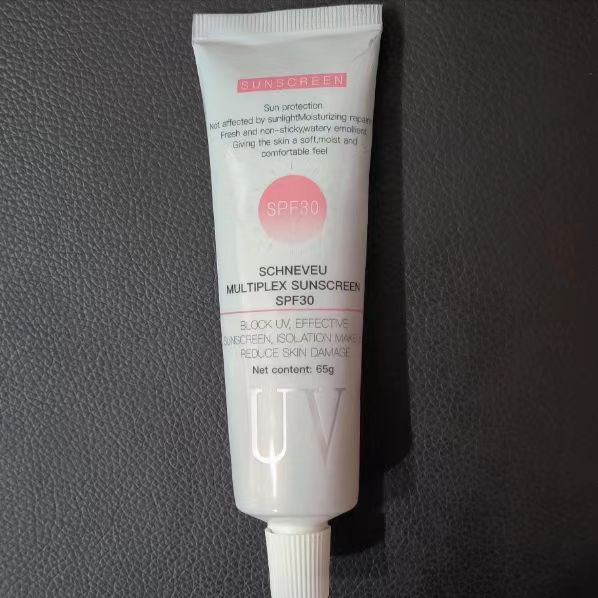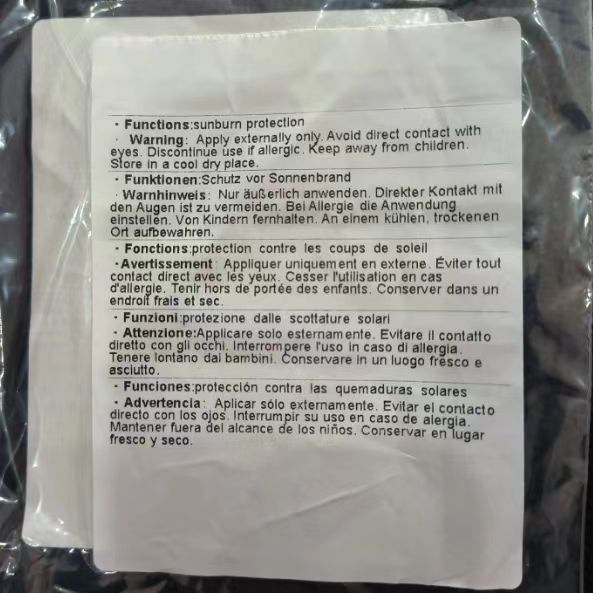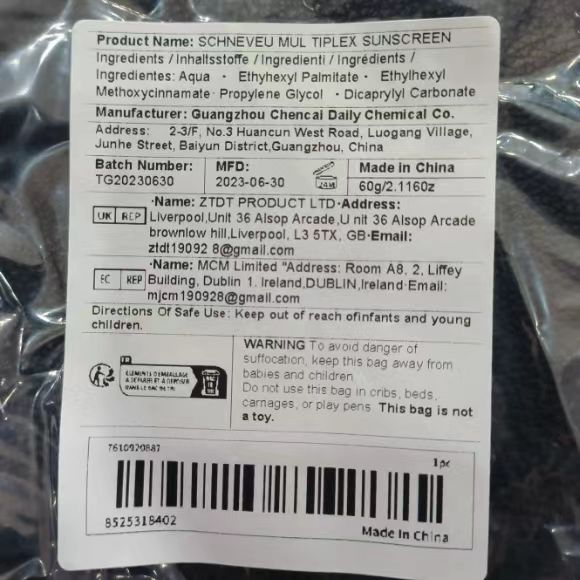 DRUG LABEL: SCHNEVEU MUL TIPLEX SUNSCREEN
NDC: 84487-002 | Form: CREAM
Manufacturer: Ruian Information Technology (Guangdong) Co., Ltd.
Category: otc | Type: HUMAN OTC DRUG LABEL
Date: 20240710

ACTIVE INGREDIENTS: ETHYL METHOXYCINNAMATE 200 mg/1 g; TITANIUM DIOXIDE 50 mg/1 g
INACTIVE INGREDIENTS: DICAPRYLYL CARBONATE 100 mg/1 g; ETHYLHEXYL PALMITATE 200 mg/1 g; 2-PHENYLPROPANAL PROPYLENE GLYCOL ACETAL 100 mg/1 g

Active ingredients

Ethylhexyl Methoxycinnamate 8.2%

Dicaprylyl Carbonate 6%

Titanium Dioxide 5%

Purpose

Sunscreen

Moisturizes throughout the day & helps protects.

Uses

Apply sunscreen generously to exposed skin. Rub it in evenly. Reapply as need, specially after swimming or sweating.

Enjoy your sun-protected day!

WARNINGS

Wamings

For exteral use only .

Do not use on damaged or broken skin.

When using this product
Only for external use. Do not ingest.
Avoid direct contact with eyes.

Stop use and ask a doctor if rash occurs .

Keep out of reach of children.

if swallowed, get medical help or contact a Poison Control Center right away.

Ask Doctor . When Pregnant or breast-feeding.

Directions
Directions for use
-apply liberally 15 minutes before sun exposure.
-reapply at least every 2 hours.
-use a water resistant sunscreen if swimming or sweating.
-Sun Protection Measures: Spending time in the sun increases your risk of skin cancer and early skin aging.
-Spectrum SPF value of 15 or higher and other sun protection：
-limit time in the sun, especially from 10 a.m.-2 p.m.,and wear long-sleeved shirts, pants, hats, and sunglasses.

Other information

Before use, read all information on the carton .

Store at controlled room temperature 20 to 25℃ (68 to 77℉) .

Inactive ingredients

Water, ethylhexyl palmitate, Ethylhexyl Methoxycinnamate, Propylene Glycol, Dioctyl Carbonate, Titanium Dioxide, Oxaline, Cetearyl Alcohol, Squalane

Additional Ingredients (Fragrances,Stabilizers,etc.)

Xanthan gum, Erythritol, Hydroxybenzyl ester